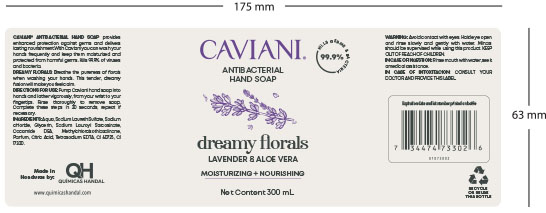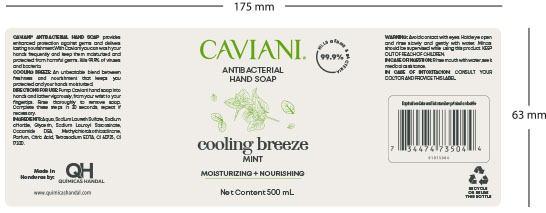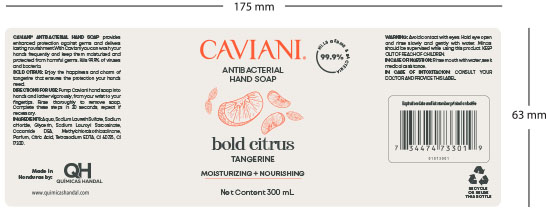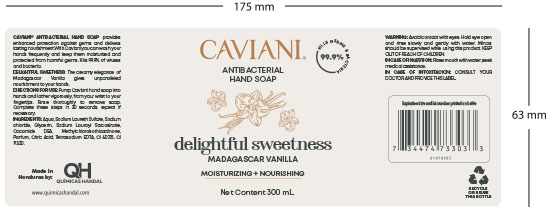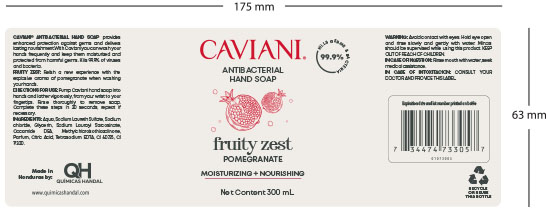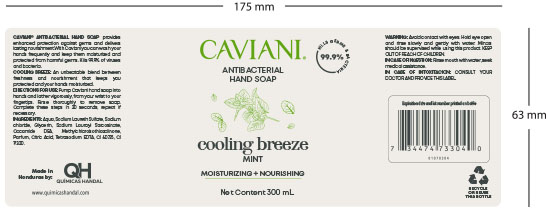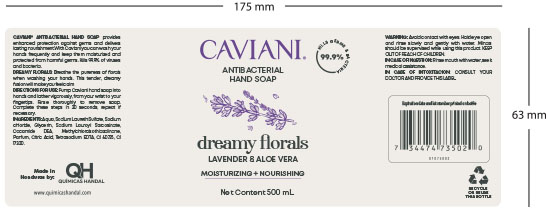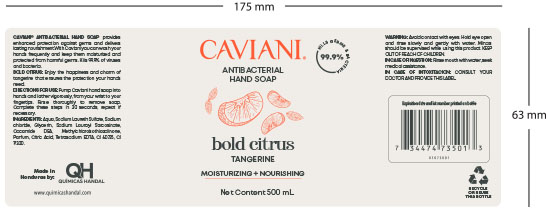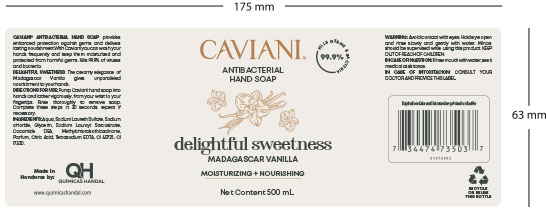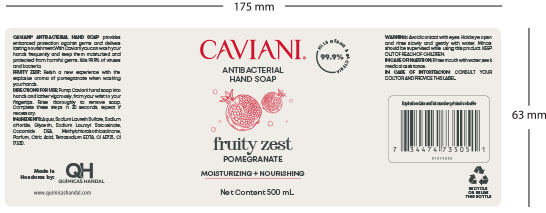 DRUG LABEL: ANTIBACTERIAL DREAMY FLORALS
NDC: 83033-0010 | Form: SOAP
Manufacturer: Quimicas Handal de Centroamerica SA de CV
Category: otc | Type: HUMAN OTC DRUG LABEL
Date: 20250108

ACTIVE INGREDIENTS: GLYCERIN 1 g/1 g
INACTIVE INGREDIENTS: WATER 1 g/1 g; SODIUM CHLORIDE 1 g/1 g; METHYLCHLOROISOTHIAZOLINONE 1 g/1 g; SODIUM LAURYL SARCOSINATE 1 g/1 g; COCO DIETHANOLAMIDE 1 g/1 g; EDETATE SODIUM 1 g/1 g; SODIUM LAURETH SULFATE 1 g/1 g

CAVIANI

DOSAGE AND ADMINISTRATION

Pump Caviani hand soap into hands and lather vigorously, from your wrist to your
fingertips. Rinse thoroughly to remove soap. Complete these steps in 20 seconds, repeat if
necessary.

INDICATIONS AND USAGE

Pump Caviani hand soap into hands and lather vigorously, from your wrist to your
fingertips. Rinse thoroughly to remove soap. Complete these steps in 20 seconds, repeat if
necessary.

WARNINGS

Avoid contact with eyes. Hold eye open
and rinse slowly and gently with water. Minors
should be supervised while using this product. KEEP
OUT OF REACH OF CHILDREN.
IN CASE OF INGESTION: Rinse mouth with water, seek
amedical assistance.
IN CASE OF INTOXICATION: CONSULT YOUR
DOCTOR AND PROVIDE THIS LABEL.

INACTIVE INGREDIENTS: Aqua, Sodium Laureth Sulfate, Sodium
chloride, Sodium Lauroyl Sarcosinate,
Cocamide DEA, Methylchloroisothiazolinone,
Paum, Citric Acid, Tetrasodium EDTA, CI 60725, CI
17200.

KEEP OUT OF REACH OF CHILDREN

Minors
should be supervised while using this product. KEEP
OUT OF REACH OF CHILDREN.

PURPOSE

enhanced protection against germs and delivers
lasting nourishment.

ACTIVE INGREDIENT

GLYCERIN